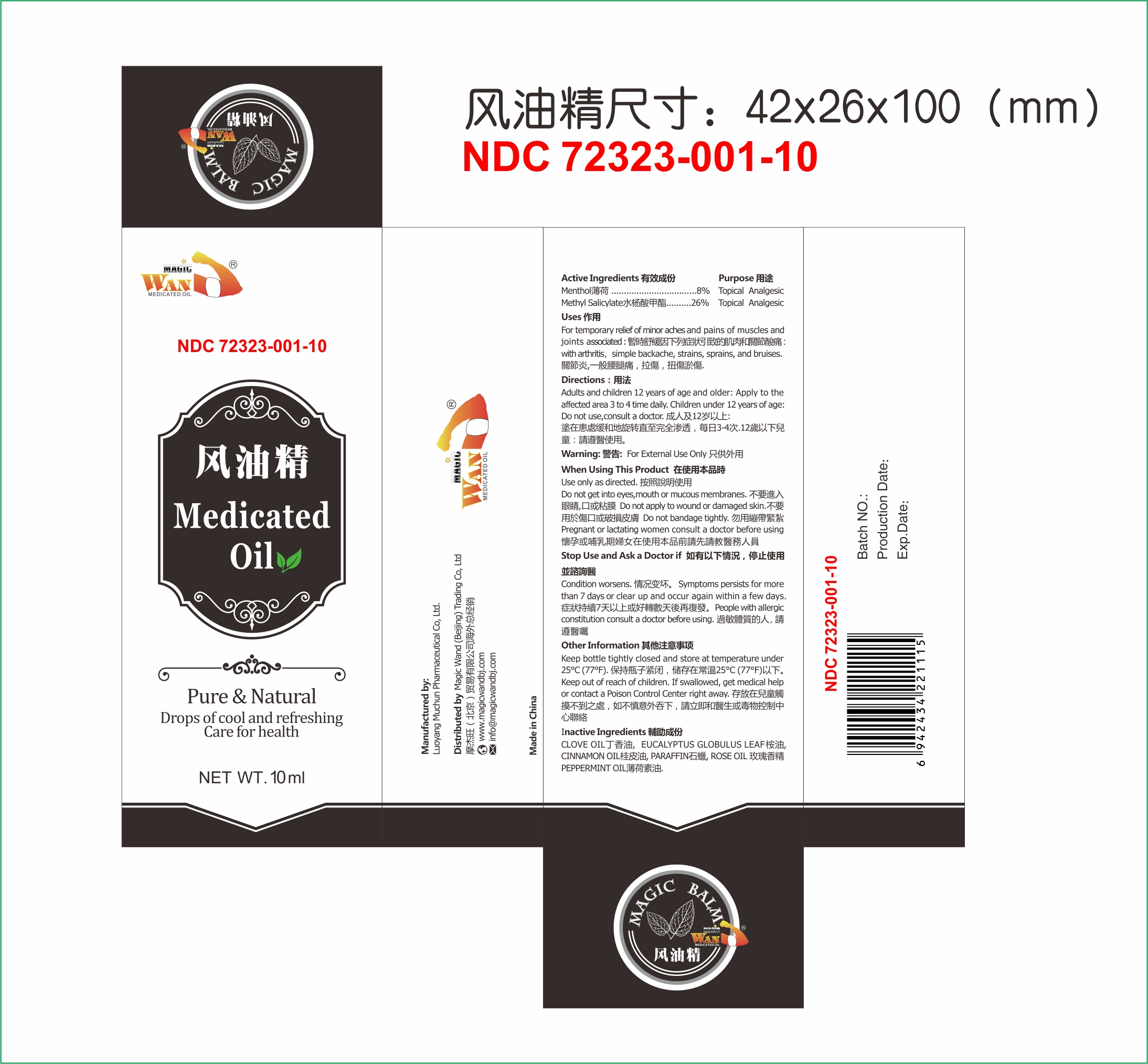 DRUG LABEL: Medicated Oil
NDC: 72323-001 | Form: OIL
Manufacturer: Luoyang Muchun Pharmaceutical Co, Ltd
Category: otc | Type: HUMAN OTC DRUG LABEL
Date: 20180705

ACTIVE INGREDIENTS: MENTHOL 8 g/100 mL; METHYL SALICYLATE 26 g/100 mL
INACTIVE INGREDIENTS: CLOVE OIL; EUCALYPTUS GLOBULUS LEAF; CINNAMON OIL; PARAFFIN; ROSE OIL; PEPPERMINT OIL

Luoyang Muchun Pharmaceutical Co, Ltd

Active Ingredients

Menthol 8%
Methyl Salicylate 26%

Purpose

Menthol Topical Analgesic
Methyl Salicylate Topical Analgesic

Uses

For temporary relief of minor aches and pains of muscles and joints associated with arthritis, simple backache, strains, sprains, and bruises.

Directions

Adults and children 12 years of age and older: Apply to the affected area 3 to 4 times daily. Children under 12 years of age: Do not use, consult a doctor.

Warning

For External Use Only.

When Using This Product

Use only as directed.
Do not get into eyes or mucous membranes.
Do not apply to wound or damaged skin.
Do not bandage tightly.
Pregnant or lactating women consult a doctor before using.

Stop Use and Ask a Doctor If

Condition worsens.
Symptoms persist for more than 7 days or clear up and occur again within a few days.
People with allergic conditution consult a doctor before using.

Other Information

Keep bottle tightly closed and store at temperature below 25°C (77°F).

Keep out of reach of children. If swallowed, get medical help or contact a Poison Control Center right away.

Manufactured by

Luoyang Muchun Pharmaceutical Co, Ltd.

Distributed by Magic Wand (Beijing) Trading Co, Ltd

1501-1502, 15th F, Building 3, No. 3 Zhonghe Road, Fengtai District, Beijing 100070

Made in China

Inactive Ingredients

CLOVE OIL, EUCALYPTUS GLOBULUS LEAF, CINNAMON OIL, PARAFFIN, ROSE OIL, PEPPERMINT OIL